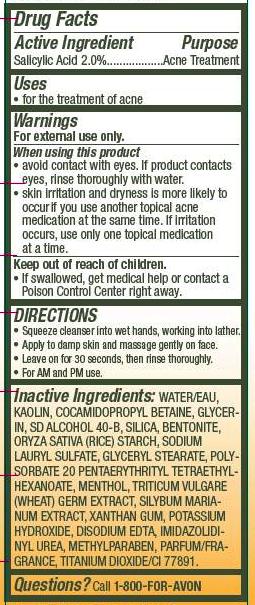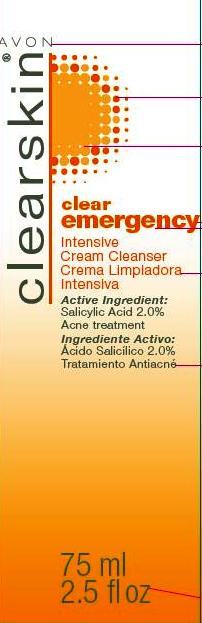 DRUG LABEL: clearskin
NDC: 10096-0277 | Form: CREAM
Manufacturer: Avon Products, Inc.
Category: otc | Type: HUMAN OTC DRUG LABEL
Date: 20120420

ACTIVE INGREDIENTS: SALICYLIC ACID 1.5 mL/75 mL

Drug Facts

Active Ingredient
Salicylic Acid 2.0%..................

Purpose
......................Acne Treatment

Uses
• for the treatment of acne

Warnings
For external use only.

When using this product

• avoid contact with eyes. If product contacts eyes, rinse thoroughly with water.
• skin irritation and dryness is more likely to occur if you use another topical acne medication at the same time. If irritation occurs, only use one topical medication at a time.

Keep out of reach of children.
• If swallowed, get medical help or contact a Poison Control Center
right away.

DIRECTIONS
• Squeeze cleanser into wet hands, working into lather.
• Apply to damp skin and massage gently on face.
• Leave on for 30 seconds, then rinse thoroughly.
• For AM and PM use.

INACTIVE INGREDIENT

Inactive Ingredients WATER/EAU, KAOLIN, COCAMIDOPROPYL BETAINE, GLYCERIN, SD ALCOHOL 40-B, SILICA, BENTONITE, ORYZA SATIVA (RICE) STARCH, SODIUM LAURYL SULFATE, GLYCERYL STEARATE, POLYSORBATE 20 PENTAERYTHRITYL TETRAETHYLHEXANOATE, MENTHOL, TRITICUM VULGARE (WHEAT) GERM EXTRACT, SILYBUM MARIANUM EXTRACT, XANTHAN GUM, POTASSIUM HYDROXIDE, DISODIUM EDTA, IMIDAZOLIDINYL UREA, METHYLPARABEN, PARFUM/FRAGRANCE, TITANIUM DIOXIDE/CI 77891.

Questions? Call 1-800-FOR-AVON